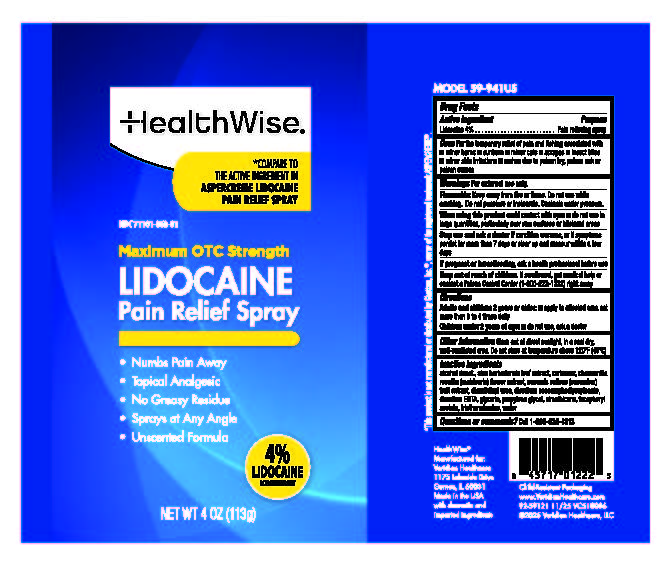 DRUG LABEL: HealthWise Lidocaine Pain Relief
NDC: 71101-068 | Form: SPRAY
Manufacturer: Veridian Healthcare
Category: otc | Type: HUMAN OTC DRUG LABEL
Date: 20251125

ACTIVE INGREDIENTS: LIDOCAINE 4 g/100 mL
INACTIVE INGREDIENTS: EDETATE DISODIUM; PROPYLENE GLYCOL; WATER; ALCOHOL; GLYCERIN; ALOE BARBADENSIS LEAF; .ALPHA.-TOCOPHEROL ACETATE; MATRICARIA CHAMOMILLA; CUCUMBER FRUIT OIL; DISODIUM COCOAMPHODIPROPIONATE; CARBOMER; TRIETHANOLAMINE; DIAZOLIDINYL UREA; PENTAMETHYLMETHOXYDISILOXANE

Healthwise 4% Lidocaine pain Relief Spray

Drug Facts

Lidocaine 4%

PURPOSE

Pain Relieving spray

Uses

for temporary relief of pain and itching associated with:

- minor burns
- sunburn
- minor cuts
- scrapes
- insect bites
- minor skin irritations
- rashes due to poison ivy, poison oak or poison sumac

Warnings

For external use only

Flammable Keep away from fire or flame. Do not use while smoking. Do not punture or incinerate. Contents under pressure.

Stop use and ask a doctor if

- condition worsens, or if symptoms persist for more than 7 days or clear up and reoccur within a few days

When using this product

• avoid spraying in eyes

• do not use in large quantities, particularly over raw surfaces or blistered areas

Keep out of reach of children.

If swallowed, get medical help or contact a Poison Control Center (1-800-222-1222) right away.

Directions

- adults and children 2 years and older:clean and dry affected area not more than 3 to 4 times daily
- children under 2 years of age:do not use, ask a doctor

Other information

Store out of direct sunlight, in a cool dry, well-ventilated area. Do not store at temperature above 120F (49C)

Inactive ingredients

alcohol denat., aloe barbadensis leaf extract, carbomer, chamomilla recutita (matricaria) flower extract, cucumis sativus (cucumber) fruit extract, diazolidinyl urea, disodium cocoamphodipropionate, disodium EDTA, glycerin, propylene glycol, simethicone, tocopheryl acetate, triethanolamine, water